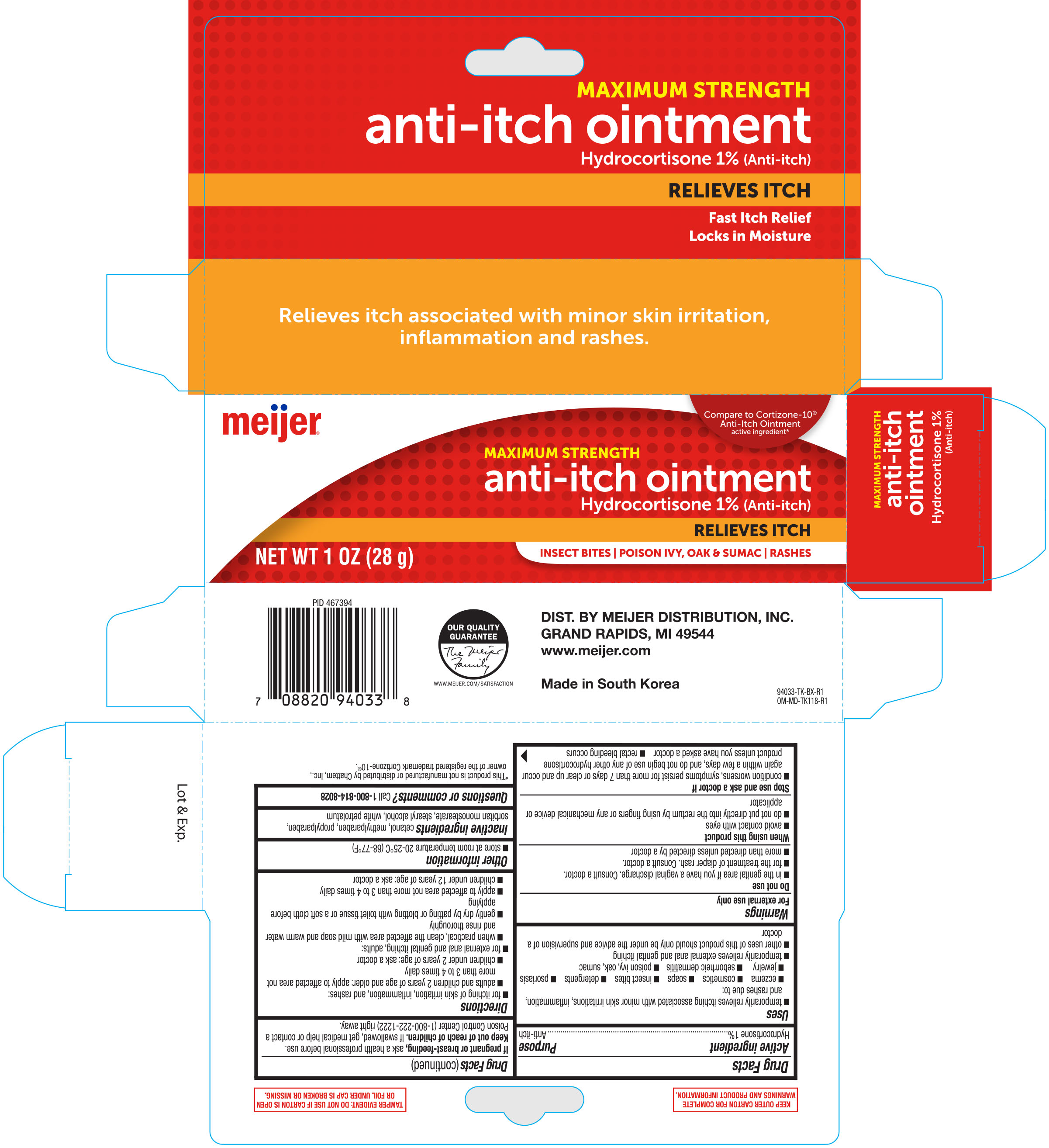 DRUG LABEL: Meijer Anti Itch
NDC: 41250-338 | Form: OINTMENT
Manufacturer: Meijer, Inc.
Category: otc | Type: HUMAN OTC DRUG LABEL
Date: 20190723

ACTIVE INGREDIENTS: HYDROCORTISONE 1 g/100 g
INACTIVE INGREDIENTS: PROPYLPARABEN; SORBITAN MONOSTEARATE; STEARYL ALCOHOL; PETROLATUM; CETYL ALCOHOL; METHYLPARABEN

Meijer Anti-itch Ointment 1oz 94033 (2019)

Active ingredient Purpose

Hydrocortisone 1%............................................................ Anti-itch

Uses

- temporary relieves itching associated with minor skin irritations, inflammation and rashes due to eczema, insect bites, poison ivy, poison oak, poison sumac, soaps, detergents, cosmetics, jewelry, seborrheic dermatitis, and psoriasis
- temporarily relieves external anal and genital itching
- other uses of this product should only be under the advice and supervision of a doctor

Warnings

For external use only

Do not use

- in the genital area if you have a vaginal discharge. Consult a doctor
- for the treatment of diaper rash. Consult a doctor
- more than directed unless directed by a doctor

When using this product

- avoid contact with the eyes
- do not put directly into the rectum by using fingers or any mechanical device or applicator

Stop use and ask a doctor if

- condition worsens, or if symptoms persist for more than 7 days or clear up and occur again within a few days and do not begin use of any other hydrocortisone product unless you have asked a doctor
- rectal bleeding occurs

Keep out of the reach of children.

If swallowed, get medical help or contact a Poison Control Center right away.

PREGNANCY OR BREAST FEEDING

If pregnant or breast-feeding, ask a health professional before use.

Keep out of reach of children. If swallowed, get medical help or contact a Poison Control Center (1-800-222-1222) right away.

INDICATIONS AND USAGE

Direections

- for itching of skin irritation, inflammation, and rashes:
- adults and children 2 years of age and older: apply to affected area not more than 3 to 4 times daily
- children under 2 years of age: consult a doctor
- for external anal and genital itching, adults:
- when practical, clean the affected area with mild soap and warm water and rinse thoroughly
- gently dry by patting or blotting with toilet tissue or soft cloth before applying
- apply to affected area not more than 3 to 4 times daily
- children under 12 years of age: consult a doctor

Other information

- store at 20°-25°C (68°-77°F)

Inactive ingredients

cetanol, methylparaben, propylparaben, sorbitan monostearate, stearyl alcohol, white petrolatum

DOSAGE AND ADMINISTRATION

Distributed by:

Meijer Distribution, Inc.

Grand Rapids, MI 49544

Made in South Korea